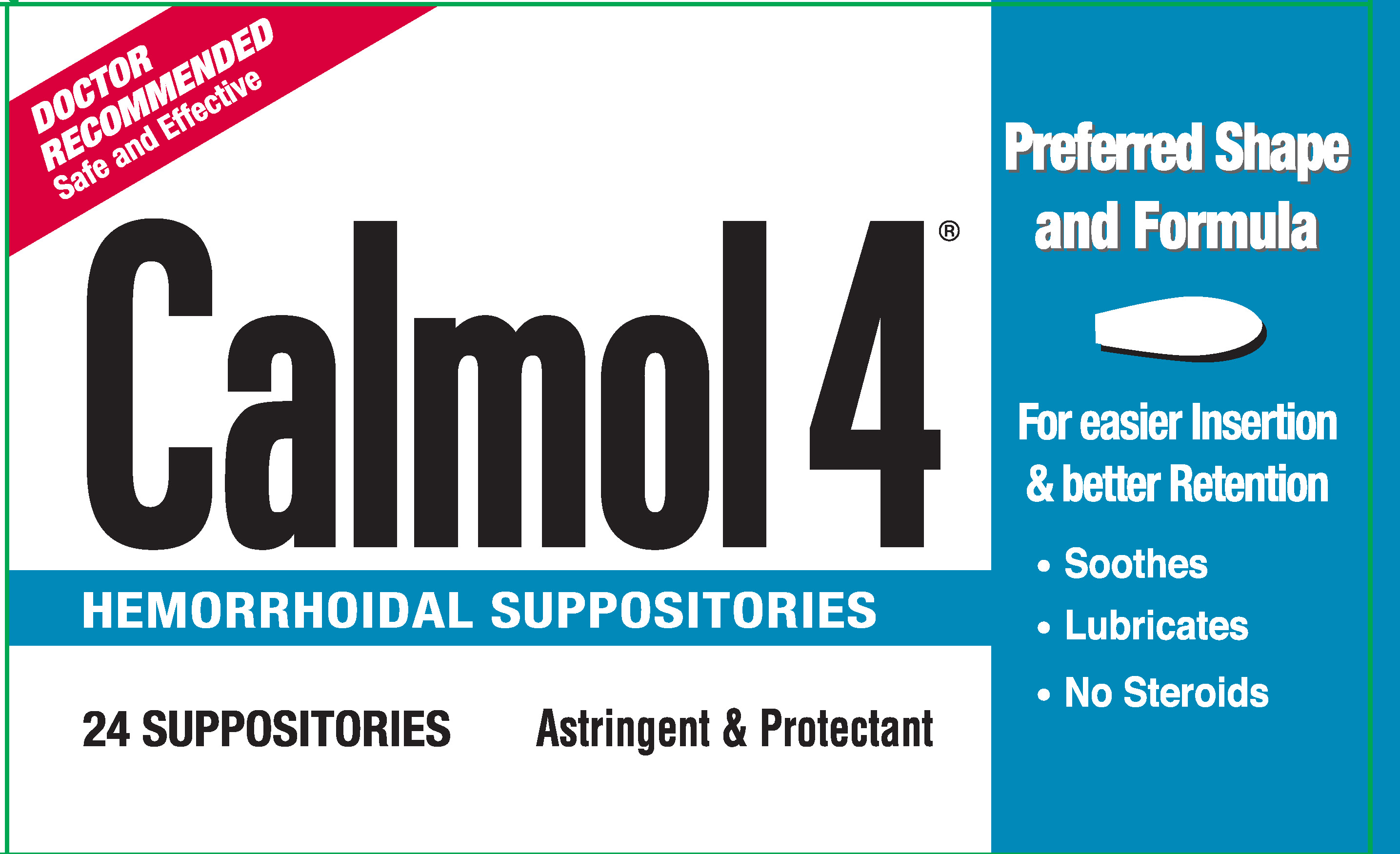 DRUG LABEL: Calmol 4
NDC: 67492-104 | Form: SUPPOSITORY
Manufacturer: Resical Inc.
Category: otc | Type: HUMAN OTC DRUG LABEL
Date: 20251024

ACTIVE INGREDIENTS: ZINC OXIDE 270 mg/1 1; COCOA BUTTER 2052 mg/1 1
INACTIVE INGREDIENTS: GLYCERYL MONOSTEARATE; FAT, HARD; METHYLPARABEN; PROPYLPARABEN; BISMUTH SUBGALLATE

Calmol 4 Suppositoires

Active Ingredients (in each suppository)

Cocoa Butter 76%

Zinc Oxide 10%

Purpose

Protectant

Astringent

Uses

- gives temporary relief of burning, irritation, itching and discomfort associated with hemorrhoids
- temporarily provides a coating for for anorectal discomforts
- temporarily protects the inflamed, irritated anorectal surface to help make bowel movements less painful

Warnings

For rectal use only

When using this product

do not exceed the recommended daily dosage unless directed by a doctor

Stop use and ask doctor if

bleeding occurs or if condition worsens or does not improve within 7 days

If pregnant or breast-feeding,

ask a health professional before use.

Keep out of reach of children.

If swallowed, get medical help or contact a Poison Control Center right away.

Directions

- adults: when practical, cleanse the affected area by patting or blotting with an appropriate cleansing pad
- gently dry by patting or blotting with toilet tissue or a soft cloth before application of this product
- detach one suppository from the strip; remove wrapper before inserting into rectum as follows:
  - slowly peel down film wrapper by pulling evenly and slowly on tabs to expose suppository
- insert 1 suppository bulb shape first into the rectum up to 6 times daily or after each bowl movement
- children under 12 years of age, consult a doctor

Other information

- store in a cool place not ober 80°F to avoid melting
- if subjected to higher temperatures, refrigeration may restore to a usable condition

Inactive ingredients

Bismuth subgallate, glyceryl stearate, hydrogenated vegetable oil, methylparaben, propylparaben

Questions or comments?

Call toll-free 1-800-204-6434 weekdays 9 AM to 5 PM EST

Calmol 4 Suppository 24 count

CALMOL 24ct_R0625.p1.pdf

Calmol 4 Hemorrhoidal Suppository

24 count

Distributed by: Resical Inc.

Orchard Park, New York 14127

The image below depicts a representative sample of packaging that is available.